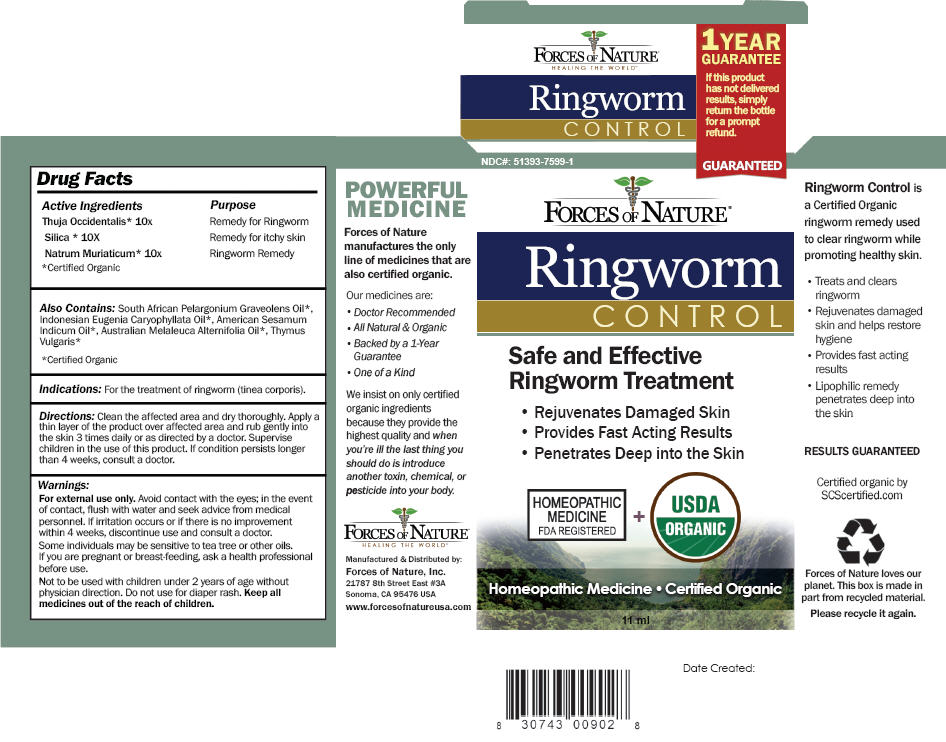 DRUG LABEL: Ringworm Control
NDC: 51393-7599 | Form: SOLUTION/ DROPS
Manufacturer: Forces of Nature
Category: homeopathic | Type: HUMAN OTC DRUG LABEL
Date: 20200428

ACTIVE INGREDIENTS: Thuja Occidentalis Leaf 10 [hp_X]/1000 mL; Silicon Dioxide 10 [hp_X]/1000 mL; Sodium Chloride 10 [hp_X]/1000 mL
INACTIVE INGREDIENTS: Sesame Oil; Tea Tree Oil; Geranium Oil, Algerian Type; Clove Oil; Thyme Oil

Ringworm
CONTROL

Drug Facts

ACTIVE INGREDIENT

Active Ingredients | Purpose
Thuja Occidentalis [Certified Organic] 10x | Remedy for Ringworm
Silica 10X | Remedy for itchy skin
Natrum Muriaticum 10x | Ringworm Remedy

Also Contains

South African Pelargonium Graveolens Oil, Indonesian Eugenia Caryophyllata Oil, American Sesamum Indicum Oil, Australian Melaleuca Alternifolia Oil, Thymus Vulgaris

Indications

For the treatment of ringworm (tinea corporis).

Directions

Clean the affected area and dry thoroughly. Apply a thin layer of the product over affected area and rub gently into the skin 3 times daily or as directed by a doctor. Supervise children in the use of this product. If condition persists longer than 4 weeks, consult a doctor.

Warnings

For external use only.

WHEN USING

Avoid contact with the eyes; in the event of contact, flush with water and seek advice from medical personnel.

STOP USE

If irritation occurs or if there is no improvement within 4 weeks, discontinue use and consult a doctor.

WHEN USING

Some individuals may be sensitive to tea tree or other oils.

PREGNANCY OR BREAST FEEDING

If you are pregnant or breast-feeding, ask a health professional before use.

DO NOT USE

Not to be used with children under 2 years of age without physician direction. Do not use for diaper rash.

KEEP OUT OF REACH OF CHILDREN

Keep all medicines out of the reach of children.

Manufactured & Distributed by:
Forces of Nature, Inc.
21787 8th Street East #3A
Sonoma, CA 95476 USA

PRINCIPAL DISPLAY PANEL - 11 ml Bottle Carton

NDC#: 51393-7599-1

GUARANTEED

FORCES OF NATURE®

Ringworm
CONTROL

Safe and Effective
Ringworm Treatment

- Rejuvenates Damaged Skin
- Provides Fast Acting Results
- Penetrates Deep into the Skin

HOMEOPATHIC
MEDICINE
FDA REGISTERED
+
USDA
ORGANIC

Homeopathic Medicine • Certified Organic

11 ml